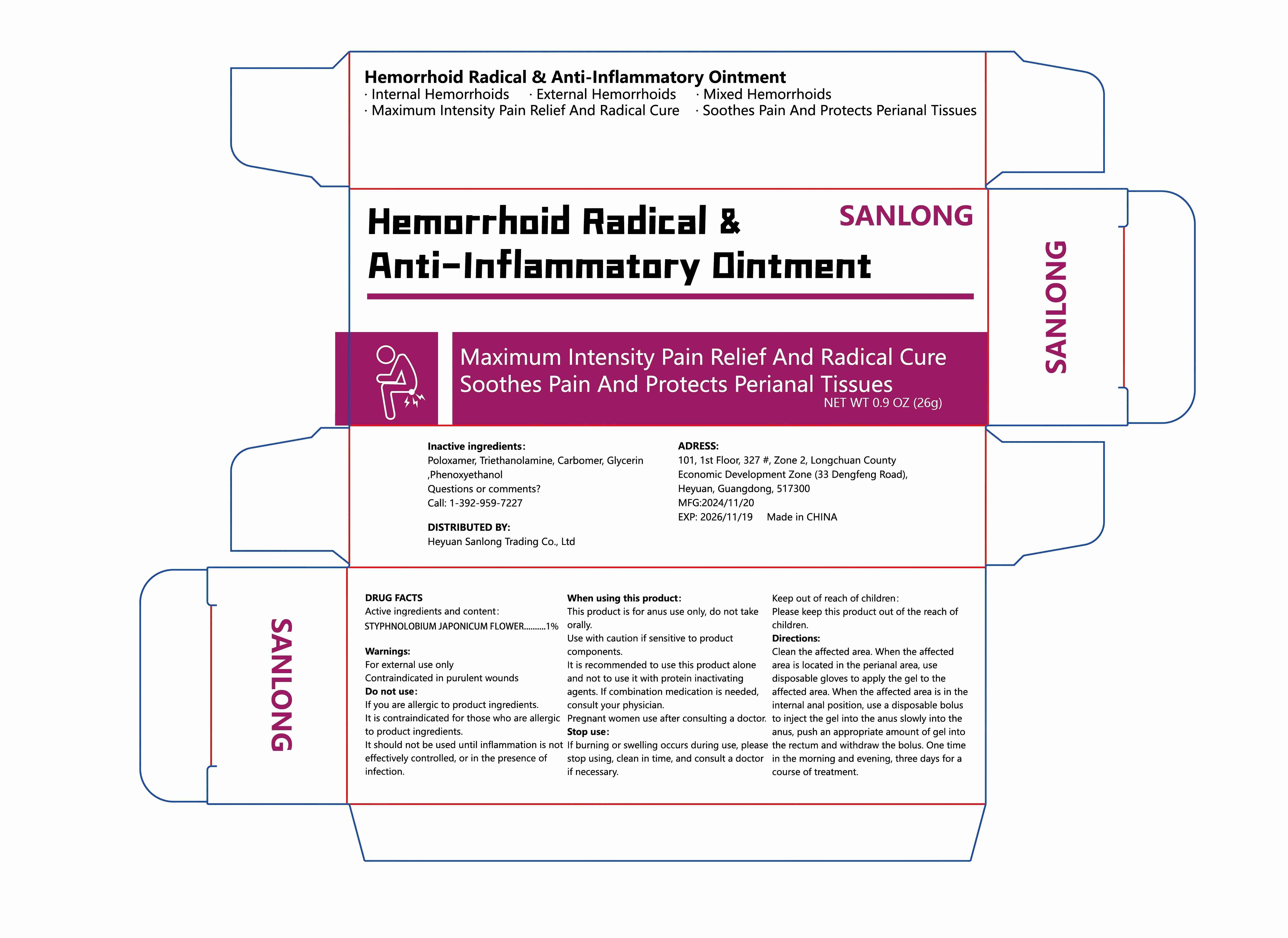 DRUG LABEL: SANLONGHemorrhoidRadicalAntilnflammatoryOintment
NDC: 85189-001 | Form: CREAM
Manufacturer: Heyuan Sanlong Trading Co., Ltd
Category: otc | Type: HUMAN OTC DRUG LABEL
Date: 20250125

ACTIVE INGREDIENTS: STYPHNOLOBIUM JAPONICUM FLOWER 1 g/100 g
INACTIVE INGREDIENTS: TRIETHANOLAMINE; GLYCERIN; CARBOMER; PLOVAMER; PHENOXYETHANOL

Active ingredients

STYPHNOLOBIUM JAPONICUM FLOWER 1%

Purpose

Treating hemorrhoids

Uses

Clean the affected area. When the affectedarea is located in the perianal area, usedisposable gloves to apply the gel to theaffected area. When the affected area is in theinternal anal position, use a disposable bolusto inject the gel into the anus slowly into theanus, push an appropriate amount of gel intothe rectum and withdraw the bolus. One timein the morning and evening, three days for acourse of treatment.

Warnings

For external use only Contraindicated in purulent wounds

Dosage and administration

This product is for anus use only, do not takeorally.Use with caution if sensitive to productcomponents.It is recommended to use this product aloneand not to use it with protein inactivatingagents. lf combination medication is needed,consult your physician.Pregnant women use after consulting a doctor.

Do not use

For external use only Contraindicated in purulent wounds

When using section

Clean the affected area. When the affectedarea is located in the perianal area, usedisposable gloves to apply the gel to theaffected area. When the affected area is in theinternal anal position, use a disposable bolusto inject the gel into the anus slowly into theanus, push an appropriate amount of gel intothe rectum and withdraw the bolus. One timein the morning and evening, three days for acourse of treatment.

stop use

This product is for anus use only, do not takeorally.Use with caution if sensitive to productcomponents.It is recommended to use this product aloneand not to use it with protein inactivatingagents. lf combination medication is needed,consult your physician.Pregnant women use after consulting a doctor.

Keep out of reach of children.

If burning or swelling occurs during use, pleasestop using, clean in time, and consult a doctorif necessary.

Keep out of reach of children:Please keep this product out of the reach ofchildren.

Inactive ingredients

Poloxamer, Triethanolamine, Carbomer, Glycerin,Phenoxyethanol